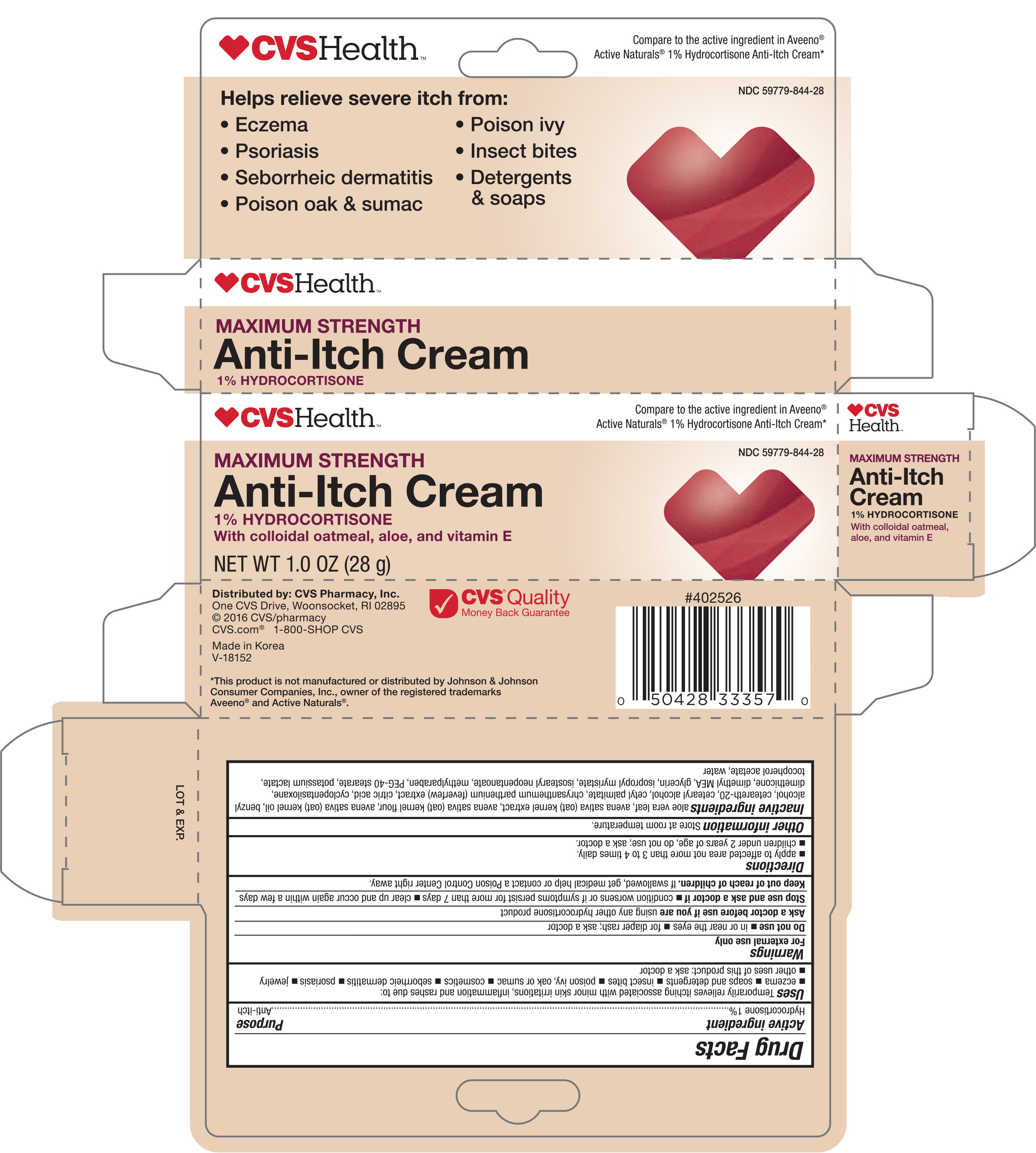 DRUG LABEL: CVS Anti-Itch Hydrocortisone
NDC: 59779-844 | Form: CREAM
Manufacturer: CVS Pharmacy, Inc.
Category: otc | Type: HUMAN OTC DRUG LABEL
Date: 20160912

ACTIVE INGREDIENTS: HYDROCORTISONE 1 mg/1 g
INACTIVE INGREDIENTS: ALOE VERA LEAF; OAT; OATMEAL; OAT KERNEL OIL; BENZYL ALCOHOL; POLYOXYL 20 CETOSTEARYL ETHER; CETYL PALMITATE; TANACETUM PARTHENIUM; CITRIC ACID MONOHYDRATE; CYCLOMETHICONE 5; DIMETHICONE; DEANOL; GLYCERIN; ISOPROPYL MYRISTATE; ISOSTEARYL MYRISTATE; ISOSTEARYL NEOPENTANOATE; METHYLPARABEN; PEG-40 STEARATE; POTASSIUM LACTATE; .ALPHA.-TOCOPHEROL ACETATE; WATER

Avtive ingredient Purpose

Hydrocortisone 1%............................. Anti-itch

Uses

Temporarily relieves itching associated with minor skin irritations, inflammation and rashes due to:

- eczema
- insect bites
- poison ivy, oak, or sumac
- soaps and detergents
- cosmetics
- jewlery
- seborrheic dematitis
- psoriasis
- other use of this product; ask a doctor

Warnings

For external use only

Do not use

- in or near the eyes
- for diaper rash: ask a doctor

Ask a doctor before use if you are using any other hydrocoritsone product

Stop use and ask a doctor

- condition worsens or if symptoms persist for more than 7 days
- symptoms last more than 7 days or clear up and occur again within a few days

Keep out of reach of children. If swallowed, get medical help or contact a Poision Control Center right away

Directions

- apply to affected area no more than 3 to 4 times daily
- children under 2 years, do not use: ask a doctor

Other information

Store at room temperature. Protect from freezing and excessive heat.

Inactive ingredients

aloe vera leaf, avena sativa (oat) kennel extract, avena sativa (oat) kennel flour, avena sativa (oast) kernel oil, benzyl alcohol, cetearth-20, cetearyl alcohol, cetyl palmitate, chrysanthemum parthenium (feverfew) extract, citric acid, cyclopentasiloxane, dimethicone, dimethyl MEA, glycerin, isopropyl myristate, isostearyl neopentanoate, methylparaben, PEG-40 stearate, potassium lactate, tocopherol acetate, water

DOSAGE AND ADMINISTRATION

DISTRIBUTED BY:

ONE CVS DRIVE

WOONSOCKET, RI 02895 USA